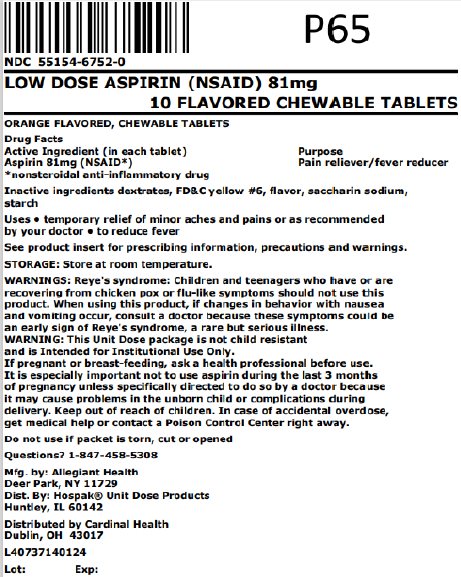 DRUG LABEL: Childrens Aspirin
NDC: 55154-6752 | Form: TABLET, CHEWABLE
Manufacturer: Cardinal Health 107, LLC
Category: otc | Type: HUMAN OTC DRUG LABEL
Date: 20241107

ACTIVE INGREDIENTS: ASPIRIN 81 mg/1 1
INACTIVE INGREDIENTS: DEXTRATES; FD&C YELLOW NO. 6; SACCHARIN SODIUM ANHYDROUS; STARCH, CORN

Low Strength Aspirin (NSAID) 81 mg

Drug Facts

HOSPAK® UNIT DOSE PRODUCTS

LOW STRENGTH ASPIRIN (NSAID)

81 mg

ORANGE FLAVORED, CHEWABLE TABLETS

FOR INSTITUTIONAL USE ONLY

Active ingredient (in each tablet)

Aspirin 81 mg (NSAID*)

*nonsteroidal anti-inflammatory drug

Purpose

Pain reliever/fever reducer

Keep Out of Reach of Children

Keep out of the reach of children. In case of accidental overdose, get medical help or contact a Poison Control Center right away.

Uses

Temporary relief of minor aches and pains or as recommended by your doctor

to reduce fever

Warnings

Reye's syndrome: Children and teenagers who have or are recovering from chicken pox or flu-like symptoms should not use this product. When using this product, if changes in behavior with nausea and vomiting occur, consult a doctor because these symptoms could be an early sign of Reye's syndrome, a rare but serious illness.

Allergy Alert: Aspirin may cause a severe allergic reaction which may include hives, facial swelling, asthma (wheezing), shock.

Stomach Bleeding Warning: This product contains an NSAID, which may cause severe stomach bleeding. The chance is higher if you ·are age 60 or older · have had stomach ulcers or bleeding problems ·take a blood thinning (anticoagulant) or steroid drug ·take other drugs containing prescription or nonprescription NSAIDs (aspirin, ibuprofen, naproxen, or others) ·have 3 or more alcoholic drinks every day while using this product ·take more or for a longer time than directed.

Do not use -if you are allergic to aspirin or any other pain reliever/fever reducer -this product for at least 7 days after tonsillectomy or oral surgery unless directed by doctor.

Ask a doctor before use if -stomach bleeding warning applies to you -you have a history of stomach problems, such as heartburn -you have high blood pressure, heart disease, liver cirrhosis, or kidney disease -you are taking a diuretic -you have asthma

Ask a doctor or pharmacist before use if you are taking a prescription drug for ·gout ·diabetes ·arthritis

Stop use and ask a doctor if ·an allergic reaction occurs. Seek medical help right away ·you experience any of the following signs of stomach bleeding ; feel faint, vomit blood, have bloody or black stools, have stomach pain that does not get better ·pain gets worse or lasts for more than 10 days ·redness or swelling is present ·new symptoms occur ·ringing in the ears or loss of hearing occurs ·You may report side effects to 1-888-952-0050.

If pregnant or breast-feeding, ask a health professional before use. It is especially important not to use aspirin during the last 3 months of pregnancy unless specifically directed to do so by a doctor because it may cause problems in the unborn child or complications during delivery.

Directions

·Drink a full glass of water with each dose ·adults and children 12 years and over: take 4 to 8 tablets every 4 hours not to exceed 48 tablets in 24 hours unless directed by doctor ·children under 12 years: consult a doctor

Inactive ingredients

dextrates, FD&C yellow #6, flavor, saccharin sodium, starch

Storage

Store at room temperature. Do not use if packet is torn, cut or opened.

Questions? 1-847-458-5308

Mfg. by: Allegiant Health, Deer Park, NY 11729

Dist. By: Hospak® Unit Dose Products, Huntley, IL 60142

Hospak is a trademark owned by its respective owner.

Distributed By:

Cardinal Health

Dublin, OH 43017

L40737140124

Rev. 08/17

Principal Display Panel

LOW DOSE ASPIRIN (NSAID) 81mg

10 FLAVORED CHEWABLE TABLETS